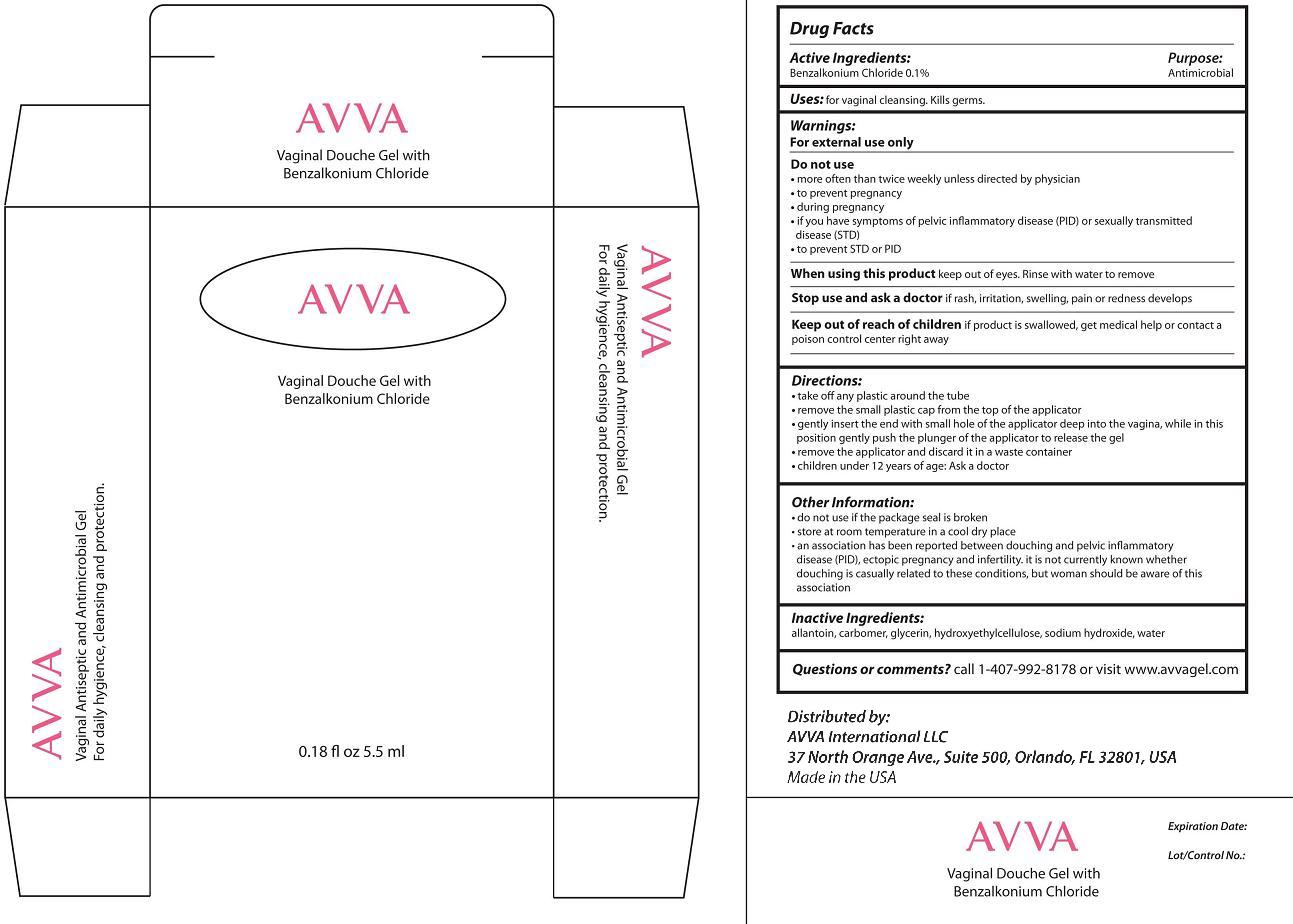 DRUG LABEL: AVVA
NDC: 42891-4148 | Form: GEL
Manufacturer: AVVA International LLC
Category: otc | Type: HUMAN OTC DRUG LABEL
Date: 20220114

ACTIVE INGREDIENTS: BENZALKONIUM CHLORIDE 100 mg/100 mL
INACTIVE INGREDIENTS: ALLANTOIN; CARBOMER HOMOPOLYMER TYPE B (ALLYL SUCROSE CROSSLINKED); GLYCERIN; HYDROXYETHYL CELLULOSE (4000 MPA.S AT 1%); SODIUM HYDROXIDE; WATER

Drug Facts

Active ingredients
Benzalkonium Chloride 0.1%

Purpose
Antimicrobial

Keep out of reach of children if product is swallowed, get medical help or contact a poison control center right away

INDICATIONS AND USAGE

Uses: for vaginal cleansing. Kills germs.
Directions:
· take of any plastic around the tube
· remove the small plastic cap from the top of the applicator
· gently insert the end with small hole of the applicator deep into the vagina, while in this position gently push the plunger of the applicator to release the gel
· remove the applicator and discard it in a waste container
· children under 12 years of age: Ask a doctor

Do not use if the package seal is broken

Warnings:
For external use only
Do not use
· more often than twice weekly unless directed by physician
· to prevent pregnancy
· during pregnancy
· if you have symptoms of pelvic inflammatory disease (PID) or sexually transmitted disease (STD)
· to prevent STD or PID
When using this product keep out of eyes. Rinse with water to remove
Stop use and ask doctor if rash, irritation, swelling, pain or redness develops

Do not use more often than twice weekly unless directed by physician

Inactive Ingredients:
allantoin, carbomer, glycerin, hydroxyethylcellulose, sodium hydroxide, water